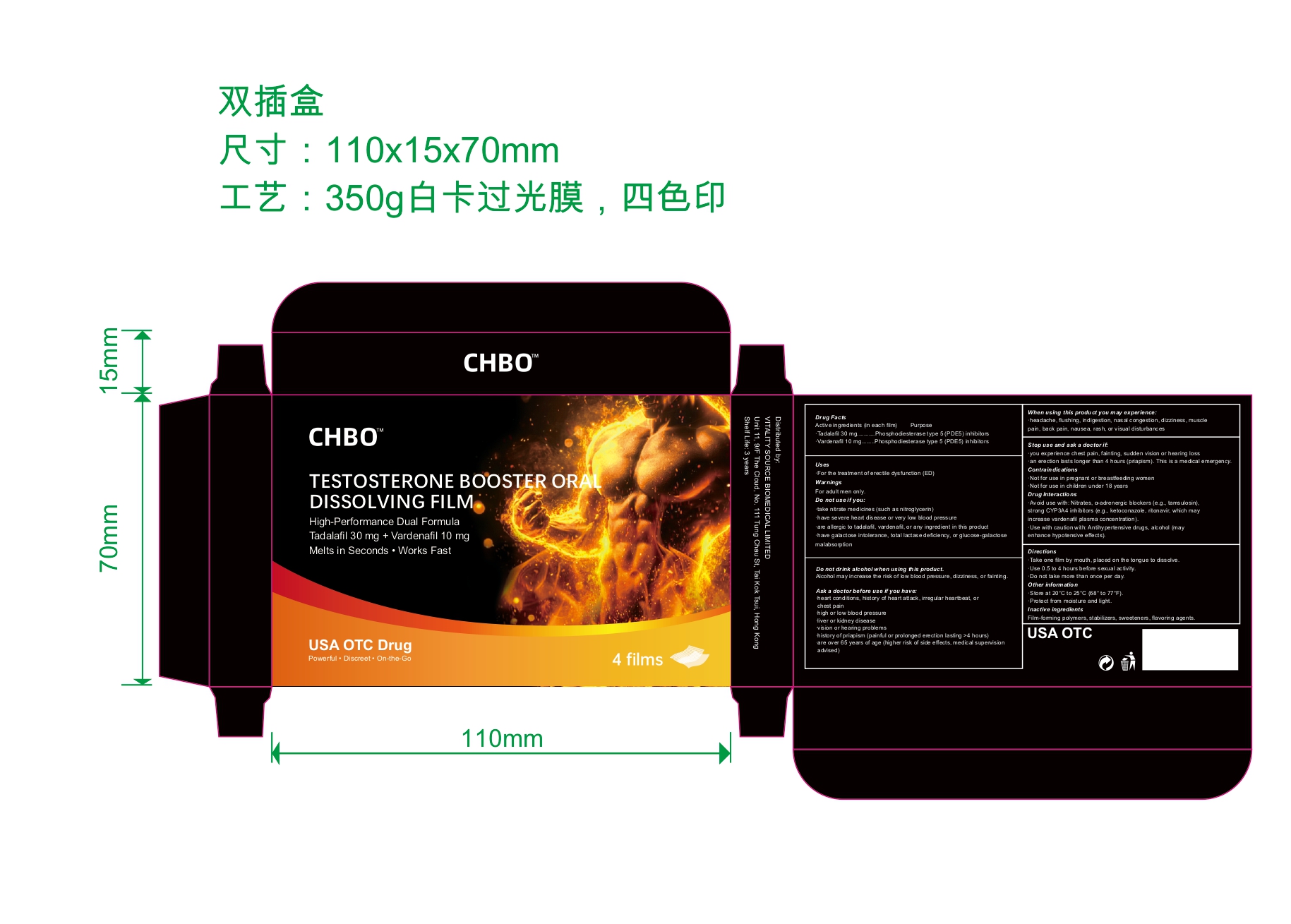 DRUG LABEL: CHBO
NDC: 87436-021 | Form: FILM, SOLUBLE
Manufacturer: Xinshu Technology Co., Limited
Category: otc | Type: HUMAN OTC DRUG LABEL
Date: 20260215

ACTIVE INGREDIENTS: VARDENAFIL 10 mg/1 1; TADALAFIL 30 mg/1 1
INACTIVE INGREDIENTS: SUCRALOSE; HYPROMELLOSES; SUCROSE

Active ingredients (in each film)

Tadalafil 30 mg

Vardenafil 10 mg

Purpose

Phosphodiesterase type 5 (PDE5) inhibitors

Uses

For the treatment of erectile dysfunction (ED)

Warnings

For adult men only.

Do not use if you:

take nitrate medicines (such as nitroglycerin)
have severe heart disease or very low blood pressure
are allergic to tadalafil, vardenafil, or any ingredient in this product
have galactose intolerance, total lactase deficiency, or glucose-galactose malabsorption

Ask a doctor before use if you have:

heart conditions, history of heart attack, irregular heartbeat, or chest pain
high or low blood pressure
liver or kidney disease
vision or hearing problems
history of priapism (painful or prolonged erection lasting >4 hours)
are over 65 years of age (higher risk of side effects, medical supervision advised)

Dosage and Administration

Take one film by mouth, placed on the tongue to dissolve.
Use 0.5 to 4 hours before sexual activity.
Do not take more than once per day.

When using this product you may experience:

headache, flushing, indigestion, nasal congestion, dizziness, muscle pain, back pain, nausea, rash, or visual disturbances

Stop use and ask a doctor if:

you experience chest pain, fainting, sudden vision or hearing loss
an erection lasts longer than 4 hours (priapism). This is a medical emergency.

Drug Interactions

Avoid use with: Nitrates, α-adrenergic blockers (e.g., tamsulosin), strong CYP3A4 inhibitors (e.g., ketoconazole, ritonavir, which may increase vardenafil plasma concentration).
Use with caution with: Antihypertensive drugs, alcohol (may enhance hypotensive effects).

Keep out of reach of children

Contraindications

Not for use in pregnant or breastfeeding women
Not for use in children under 18 years

Inactive ingredients

Film-forming polymers, stabilizers, sweeteners, flavoring agents.